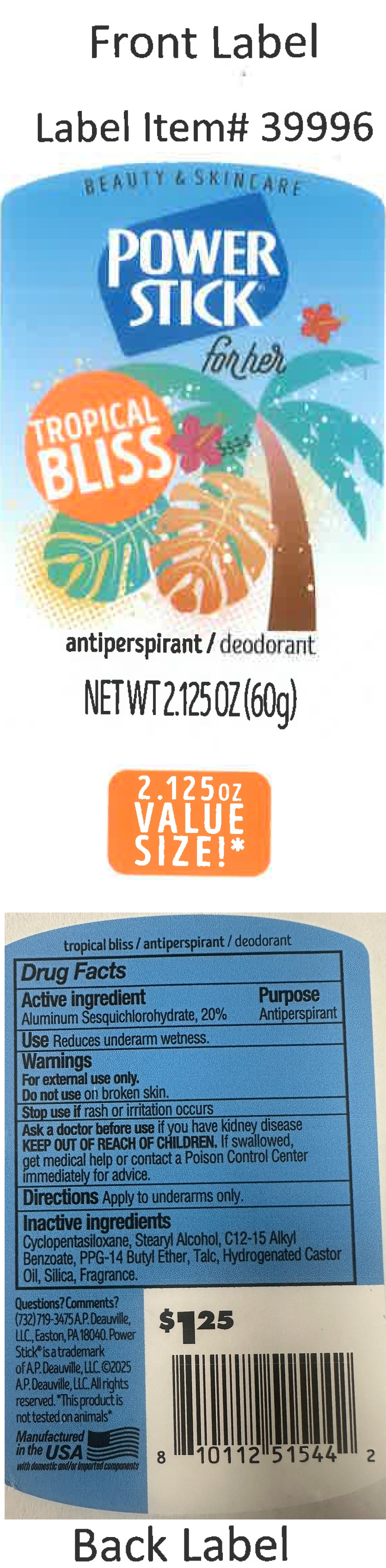 DRUG LABEL: Power Stick For Her Antiperspirant Deodorant Tropical Bliss
NDC: 42913-043 | Form: STICK
Manufacturer: A.P. Deauville, LLC
Category: otc | Type: HUMAN OTC DRUG LABEL
Date: 20250515

ACTIVE INGREDIENTS: ALUMINUM SESQUICHLOROHYDRATE 200 mg/1 g
INACTIVE INGREDIENTS: CYCLOMETHICONE 5; STEARYL ALCOHOL; ALKYL (C12-15) BENZOATE; PPG-14 BUTYL ETHER; TALC; HYDROGENATED CASTOR OIL; SILICON DIOXIDE

Power Stick For Her Antiperspirant Deodorant Tropical Bliss

Active ingredient

Aluminum Sesquichlorohydrate, 20%

Purpose

Antiperspirant

Use

Reduces underarm wetness.

Warnings

For external use only.

Do not use

on broken skin.

Stop use if

rash or irritation occurs

Ask a doctor before use

if you have kidney disease

KEEP OUT OF REACH OF CHILDREN.

If swallowed, get medical help or contact a Poison Control Center immediately for advice.

Directions

Apply to underams only.

Inactive ingredients

Cyclopentasiloxane, Stearyl Alcohol, C12-15 Alkyl Benzoate, PPG-14 Butyl Ether, Talc, Hydrogenated Castor Oil, Silica, Fragrance.

Questions? Comments?

(732) 719-3475